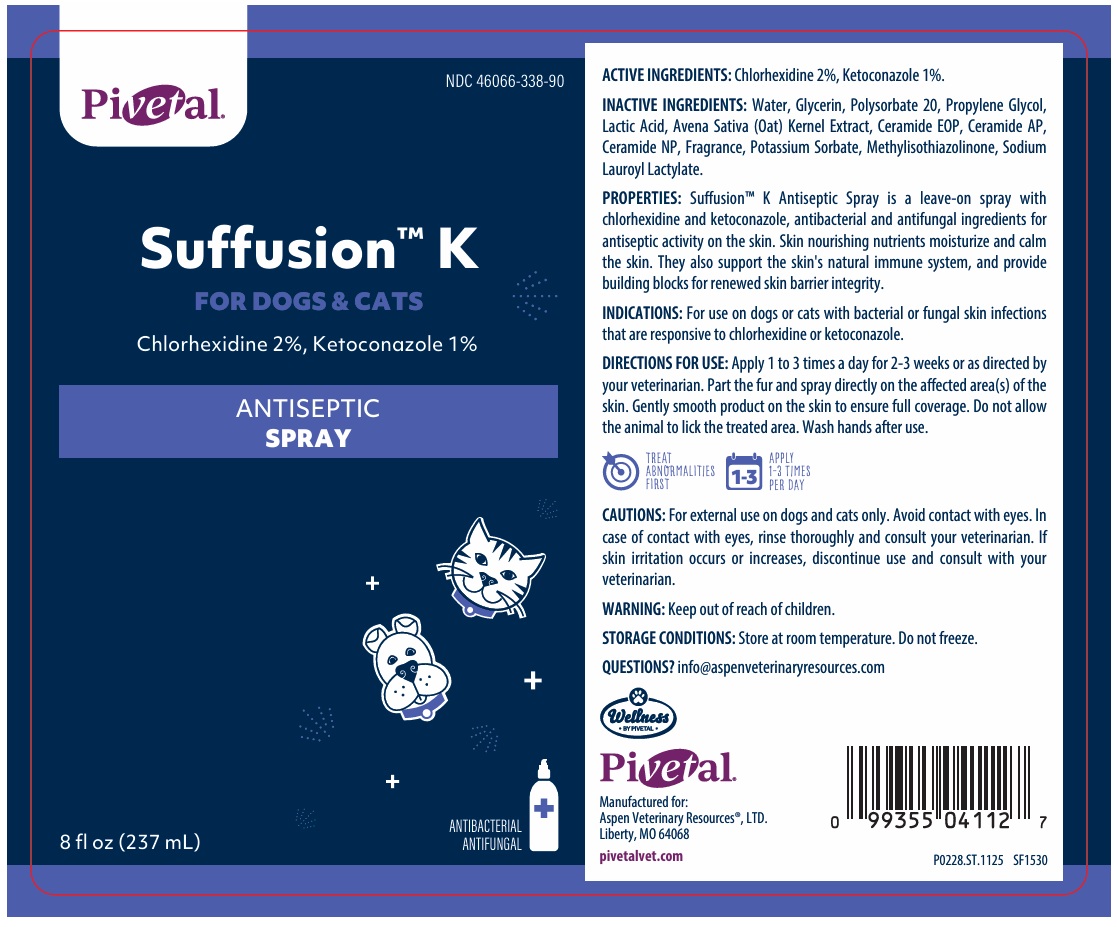 DRUG LABEL: Suffusion K ANTISEPTIC
NDC: 46066-338 | Form: SPRAY
Manufacturer: Aspen Veterinary Resources, LTD.
Category: animal | Type: OTC ANIMAL DRUG LABEL
Date: 20260212

ACTIVE INGREDIENTS: CHLORHEXIDINE 2 g/100 mL; KETOCONAZOLE 1 g/100 mL
INACTIVE INGREDIENTS: WATER; GLYCERIN; POLYSORBATE 20; PROPYLENE GLYCOL; LACTIC ACID, UNSPECIFIED FORM; OAT; CERAMIDE 9; CERAMIDE AP; CERAMIDE NP; POTASSIUM SORBATE; METHYLISOTHIAZOLINONE; SODIUM LAUROYL LACTYLATE

Pivetal® Suffusion™ K ANTISEPTIC SPRAY

ACTIVE INGREDIENTS:

Chlorhexidine 2%, Ketoconazole 1%.

INACTIVE INGREDIENTS:

Water, Glycerin, Polysorbate 20, Propylene Glycol, Lactic Acid, Avena Sativa (Oat) Kernel Extract, Ceramide EOP, Ceramide AP, Ceramide NP, Fragrance, Potassium Sorbate, Methylisothiazolinone, Sodium Lauroyl Lactylate.

PROPERTIES:

SuffusionTM K Antiseptic Spray is a leave-on spray with chlorhexidine and ketoconazole, antibacterial and antifungal ingredients for antiseptic activity on the skin. Skin nourishing nutrients moisturize and calm the skin. They also support the skin's natural immune system, and provide building blocks for renewed skin barrier integrity.

INDICATIONS:

For use on dogs or cats with bacterial or fungal skin infections that are responsive to chlorhexidine or ketoconazole.

DIRECTIONS FOR USE:

Apply 1 to 3 times a day for 2-3 weeks or as directed by your veterinarian. Part the fur and spray directly on the affected area(s) of the skin. Gently smooth product on the skin to ensure full coverage. Do not allow the animal to lick the treated area. Wash hands after use.

TREAT ABNORMALITIES FIRST

APPLY 1-3 TIMES PER DAY

CAUTIONS:

For external use on dogs and cats only. Avoid contact with eyes. In case of contact with eyes, rinse thoroughly and consult your veterinarian. If skin irritation occurs or increases, discontinue use and consult with your veterinarian.

WARNING:

Keep out of reach of children.

STORAGE CONDITIONS:

Store at room temperature. Do not freeze.

QUESTIONS?

info@aspenveterinaryresources.com

FOR DOGS & CATS

ANTIBACTERIAL
ANTIFUNGAL

Manufactured for:
Aspen Veterinary Resources®, LTD.
Liberty, MO 64068

pivetalvet.com